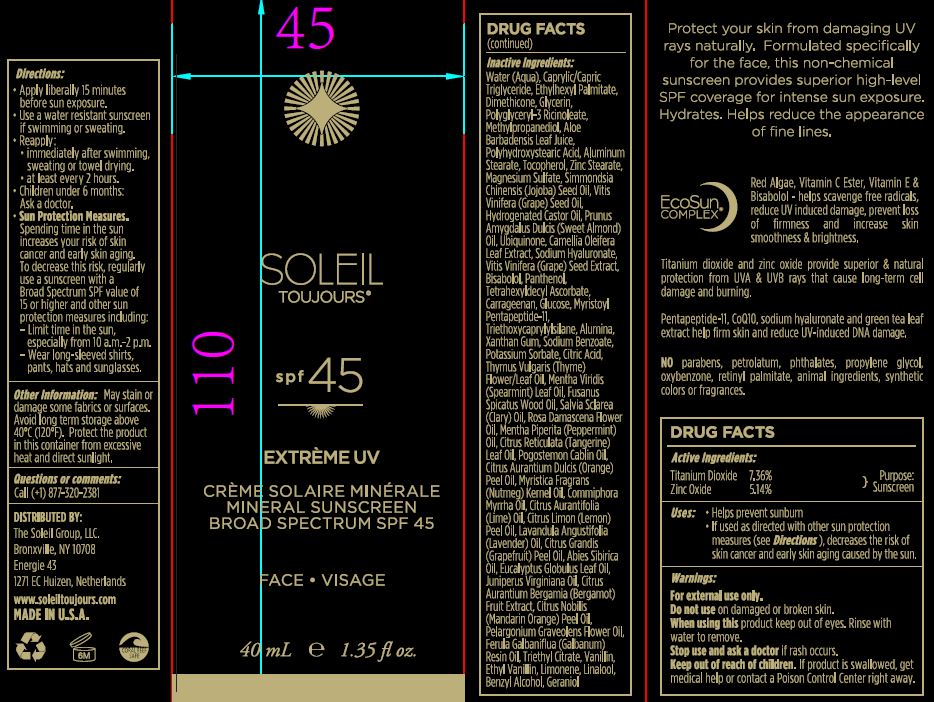 DRUG LABEL: Mineral Sunscreen Broad Spectrum SPF 45
NDC: 62742-4152 | Form: CREAM
Manufacturer: Allure Labs, Inc
Category: otc | Type: HUMAN OTC DRUG LABEL
Date: 20171211

ACTIVE INGREDIENTS: ZINC OXIDE 51.4 mg/1 mL; TITANIUM DIOXIDE 73.6 mg/1 mL
INACTIVE INGREDIENTS: WATER; MEDIUM-CHAIN TRIGLYCERIDES; ETHYLHEXYL PALMITATE; DIMETHICONE; GLYCERIN; POLYGLYCERYL-3 RICINOLEATE; METHYLPROPANEDIOL; aloe; POLYHYDROXYSTEARIC ACID (2300 MW); ALUMINUM STEARATE; TOCOPHEROL; ZINC STEARATE; MAGNESIUM SULFATE, UNSPECIFIED FORM; SIMMONDSIA CHINENSIS SEED; VITIS VINIFERA SEED; HYDROGENATED CASTOR OIL; ALMOND OIL; UBIQUINONE Q2; CAMELLIA OLEIFERA LEAF; HYALURONATE SODIUM; .ALPHA.-BISABOLOL, (+)-; PANTHENOL; TETRAHEXYLDECYL ASCORBATE; CARRAGEENAN; DEXTROSE, UNSPECIFIED FORM; TRIETHOXYCAPRYLYLSILANE; ALUMINUM OXIDE; XANTHAN GUM; SODIUM BENZOATE; POTASSIUM SORBATE; CITRIC ACID MONOHYDRATE; THYMUS VULGARIS LEAF; SPEARMINT OIL; CLARY SAGE OIL; SANTALUM SPICATUM OIL; ROSA DAMASCENA FLOWER OIL; PEPPERMINT OIL; CITRUS RETICULATA LEAF OIL; PATCHOULI OIL; ORANGE OIL; MYRRH OIL; LIME OIL; LEMON OIL; LAVENDER OIL; GRAPEFRUIT OIL; ABIES SIBIRICA LEAF OIL; EUCALYPTUS GLOBULUS LEAF; JUNIPERUS VIRGINIANA OIL; BERGAMOT OIL; TANGERINE; PELARGONIUM GRAVEOLENS FLOWER OIL; GALBANUM OIL; TRIETHYL CITRATE; VANILLIN; ETHYL VANILLIN; LIMONENE, (+)-; LINALOOL, (+)-; BENZYL ALCOHOL; GERANIOL

Drug Facts

ACTIVE INGREDIENT

Titanium Dioxide - 7.36%

Zinc Oxide - 5.14%

INDICATIONS AND USAGE

Helps prevent sunburn

if used as directed with other sun protection measures, decreases the risk of skin cancer and early skin aging caused by the sun.

WARNINGS

For external use only.

do not use on damaged or broken skin.

When using this product keep out of eyes. Rinse with water to remove.

Stop use and ask a doctor if rash occurs.

KEEP OUT OF REACH OF CHILDREN

if product is swallowed, get medical help or contact a Poison Control Center right away.

DOSAGE AND ADMINISTRATION

apply liberally 15 minutes before sun exposure.

use a water resistant sunscreen if swimming or sweating.

reapply:

immidiately aftr swimming, sweating or towel drying.

at least every 2 hours.

children under 6months: ask doctor

Sun protection measures:

Spending time in the sun increases your risk of skin cancer and early skin aging. To decrease the risk, regularly use a sunscreen with a Broad Spectrum SPF value of 15 or higher and other sun protector measures including:

limit time in the sun, especially from 10:00 am to 2:00 pm.

wear long sleaved shirts, pants, hats and sun glasses.

OTHER SAFETY INFORMATION

May stain or damage some fabrics or surfaces. Avoid long term storage above 40C (120F). Protect the product in this container from excessive heat and direct sunlight.

INACTIVE INGREDIENT

Water (Aqua), Caprylic/Capric Triglyceride, Ethylhexyl Palmitate, Dimethicone, Glycerin, Polyglyceryl-3 Ricinoleate, Methylpropanediol, Aloe Barbadensis Leaf Juice, Polyhydroxystearic Acid, Aluminum Stearate, Tocopherol, Zinc Stearare, Magnesium Sulfate, Simmondsia Chinesis (Jojoba) Seed Oil, Vitis Vinifera (Grape) Seed Oil, Hydrogenated Castor oil, Prunus Amygdalus Dulcis (Sweet Almond) Oil, Ubiquinone, Camellia Oleifera Leaf Extract, Sodium Hyaluronate, Vitis Vinifera (Grape) Seed Extract, Bisabolol, Panthenol, Tetrahexyldecyl Ascorbate, Carrageenan, Glucose, Myristoyl Pentapeptide-11, Triethoxycaprylylsilane, Alumina, Xanthan Gum, Sodium Benzoate, Potassium Sorbate, Citric Acid, Thymus Vulgaris (Thyme) Flower/Leaf Oil, Mentha Virdis (Spearmint) Leaf Oil, Fusanus Spicatus Wood Oil, Salvia Sclarea (Clary) Oil, Rosa Damascena Flower Oil, Mentha Piperita (Peppermint) Oil, Citrus Reticulata (Tangerine) Leaf Oil, Pogostemon Cablin Oil, Citrus Aurantium Dulcis (Orange) Peel Oil, Myritica Fragrans (Nutmeg) Kernel Oil, Commiphora Myrrha Oil, Citrus Aurantifolia (Lime) Oil, Citrus Limon (Lemon) Peel Oil, Lavandula Angustifolia (Lavender) Oil, Citrus Grandis (Grapefruit) Peel oil, Abies Sibirica Oil, Eucalyptus Globulus Leaf Oil, Juniperus Virginiana Oil, Citrus Aurantium Bergamia (Bergamot) Fruit Extract, Citrus Nobilis (Mandarin Orange) Peel Oil, Pelargonium Graveolens Flower Oil, Ferula Galbaniflua (Galbanum) Resin Oil, Triethyl Citrate, Vanillin, ethyl Vanillin, Limonene, Linalool, benzyl Alcohol, Geraniol.

PACKAGE LABEL

Distributed By:

The Soleil Group, LLC.

Bronxville, NY 10708

Energie 43

1271 EC Huizen, Netherlands

www.soleiltoujours.com

MADE IN U.S.A.